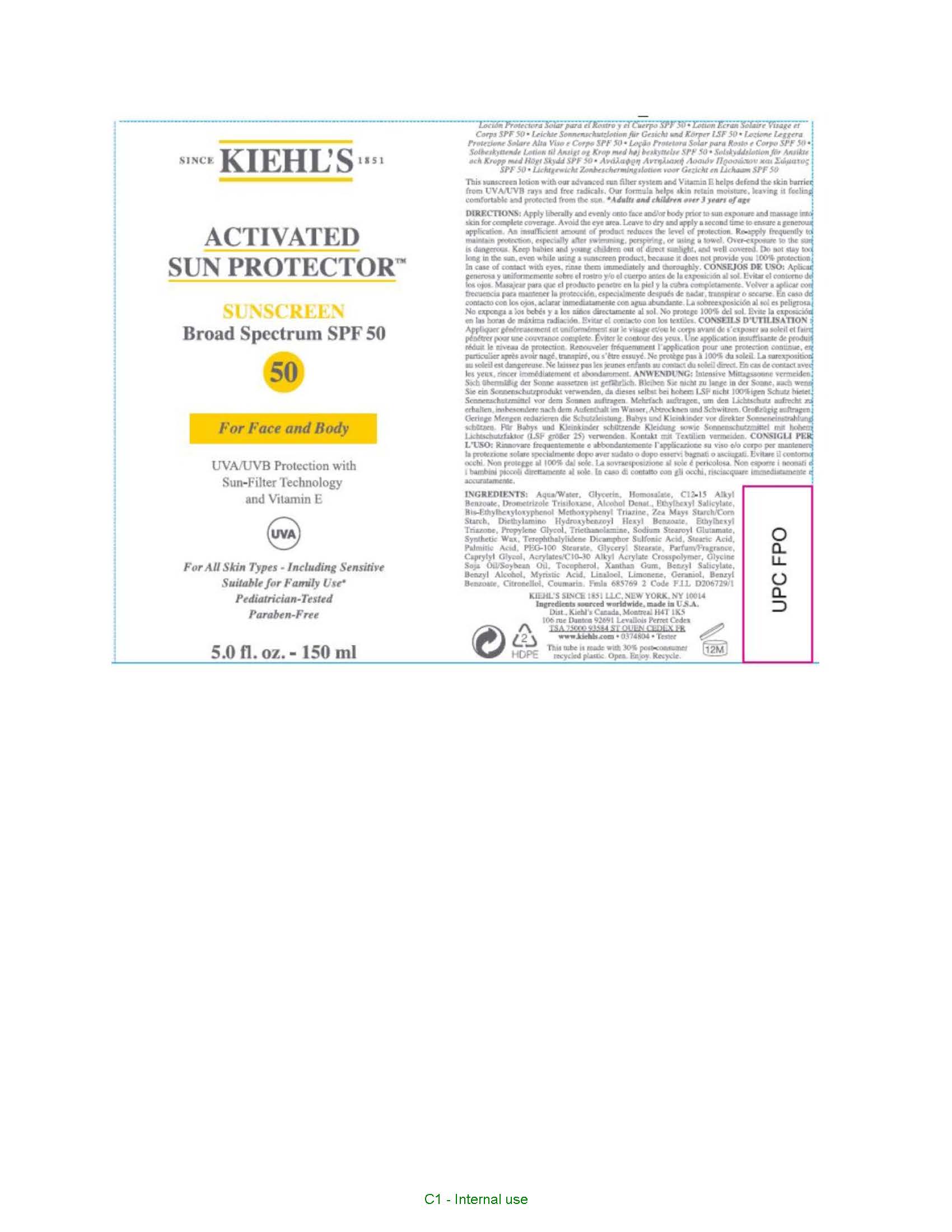 DRUG LABEL: Kiehls Activated Sun Protector Sunscreen SPF 50 For Face and Body For All Skin Types
NDC: 49967-123 | Form: LOTION
Manufacturer: L'Oreal USA Products Inc
Category: otc | Type: HUMAN OTC DRUG LABEL
Date: 20260107

ACTIVE INGREDIENTS: ETHYLHEXYL TRIAZONE 30 mg/1 mL; DROMETRIZOLE TRISILOXANE 50 mg/1 mL; HOMOSALATE 100 mg/1 mL; ECAMSULE 30 mg/1 mL; OCTISALATE 50 mg/1 mL; BEMOTRIZINOL 40 mg/1 mL; DIETHYLAMINO HYDROXYBENZOYL HEXYL BENZOATE 30 mg/1 mL
INACTIVE INGREDIENTS: WATER; GLYCERIN; ALKYL (C12-15) BENZOATE; ALCOHOL; STARCH, CORN; PROPYLENE GLYCOL; TROLAMINE; SULFURIC ACID; STEARIC ACID; PEG-100 STEARATE; CAPRYLYL GLYCOL; GLYCERYL MONOSTEARATE; SODIUM STEAROYL GLUTAMATE; SOYBEAN OIL; TOCOPHEROL; XANTHAN GUM; BENZYL SALICYLATE; BENZYL ALCOHOL; MYRISTIC ACID

Drug Facts

Directions

Apply liberally and evenly onto face and/or body prior to sun exposure and massage into skin for complete coverage. Avoid the eye area. Leave ot dry and apply a second time to ensure a generous application. An insufficient amount of product reduces the level of protection. Re-apply frequently to maintain protection, especially after swimming, perspiring, or using a towel. Over-exposure to tht sun is dangerous. Keep babies and young children out of direct sunlight, and well covered. Do not stay too long in the sun, even while using a sunscreen product, because it does not provide you 100% protection. In case of contact with eyes, rinse them immediately and thoroughly.

Ingredients

Ethylhexyl Triazone, Drometrizole Trisiloxane, Homosalate, Terephthalylidene Dicamphor Sulfonic Acid, Ethyhexyl Salicylate, Bis-Ethylhexyloxyphenol methoxyphenyl triazine, Diethylamino hydroxybenzoyl hexyl benzoate

Ingredients

Aqua/Water, Glycerin, C12-15 Alkyl Benzoate, Alcohol Denat., Zea Mays Starch/Corn Starch, Propylene Glycol, Synthetic Wax, Sulfonic Acid, Stearic Acid, Palmitic Acid, PEG-100 Stearate, Glyceryl Stearate, Parfum/Fragrance, Caprylyl Glycol, Acrylates/C10-30 Alkyl Acrylate Crosspolymer, Sodium Stearoyl Glutamate, Glycine Soja Oil/Soybean Oil, Tocopherol, Xanthan Gum, Benzyl Salicylate, Benzyl Alcohol, Myristic Acid